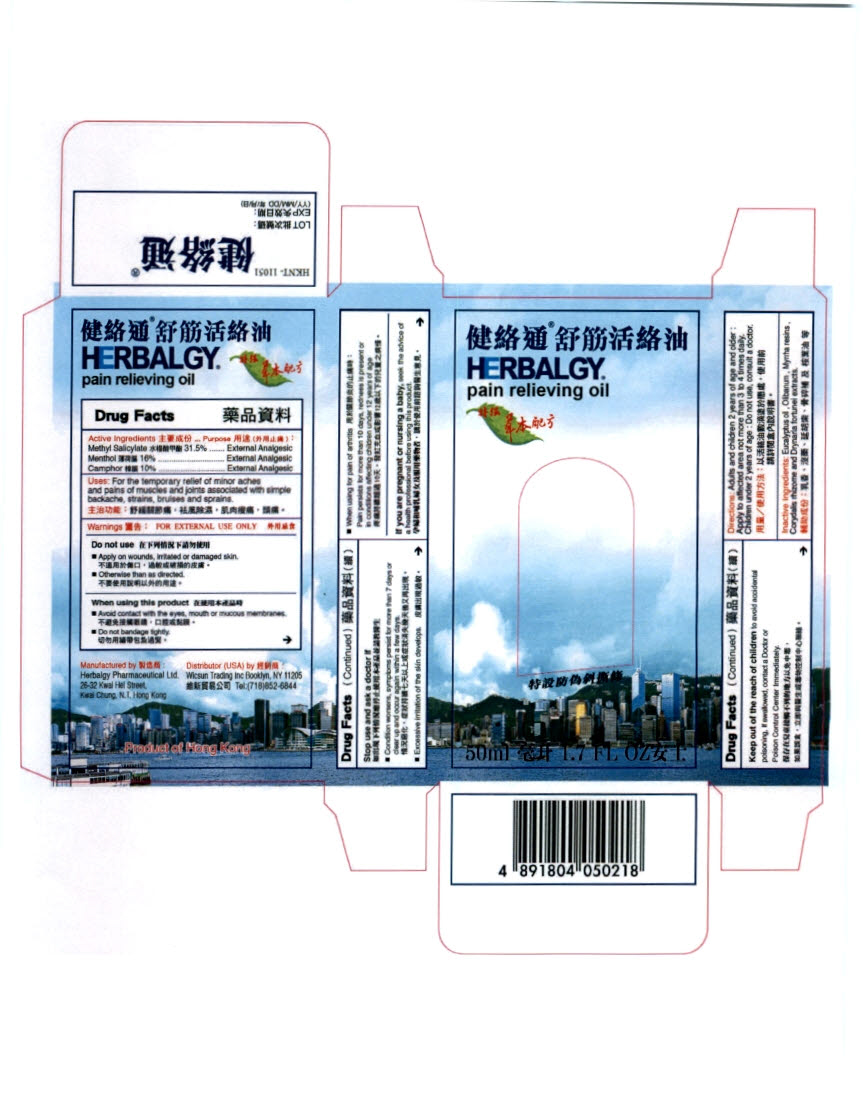 DRUG LABEL: Herbalgy
                
NDC: 66898-100 | Form: OIL
Manufacturer: Herbalgy Pharmaceutical Limited 
Category: otc | Type: HUMAN OTC DRUG LABEL
Date: 20120227

ACTIVE INGREDIENTS: CAMPHOR (SYNTHETIC) 10 mL/100 mL; MENTHOL 16 mL/100 mL; METHYL SALICYLATE 31.5 mL/100 mL
INACTIVE INGREDIENTS: EUCALYPTUS OIL; FRANKINCENSE; MYRRH; CORYDALIS YANHUSUO TUBER; DRYNARIA FORTUNEI ROOT

Drug Facts

Active Ingredients
Methyl Salicylate 31.5%
Menthol 16%
Camphor 10%

Purpose
External Analgesic
External Analgesic
External Analgesic

INDICATIONS AND USAGE

Uses: For the temporary relief of minor aches and pains of muscles and joints associated withsimple backache, strains, bruises and sprains.

Warnings: FOR EXTERNAL USE ONLY

Do not use

- Apply on wounds, irritated or damaged skin.
- Otherwise than as directed

When using this product

- Avoid contact with the eyes, mouth or mucous membranes.
- Do not bandage tightly.

Stop use and ask a doctor if:

- Condition worsens, symptoms persist for more than 7 days or clear up and occur again within a few days.
- Excessive irritation of the skin develops.
- When using this product for arthritis: Pain persists for more than 10 days, redness is present or in conditions affecting children under 12 years of age

PREGNANCY OR BREAST FEEDING

If pregnant or breast feeding, see the advise of a health professional before using this product.

Keep out of reach of children to avoid accidental poisoning. If swallowed, contact a Doctor or Poison Control Center immediately

Directions
Adults and children2 years of age and older: Apply to affected area not more than 3-4 times daily.
Children under 2 years of age: Do not use, consult a doctor

INACTIVE INGREDIENT

Inactive Ingredients: Eucalyptus oil, Olibanum, Myrhha resins, Corydalis rhizome and Drynaria fortunei extracts

Package Label